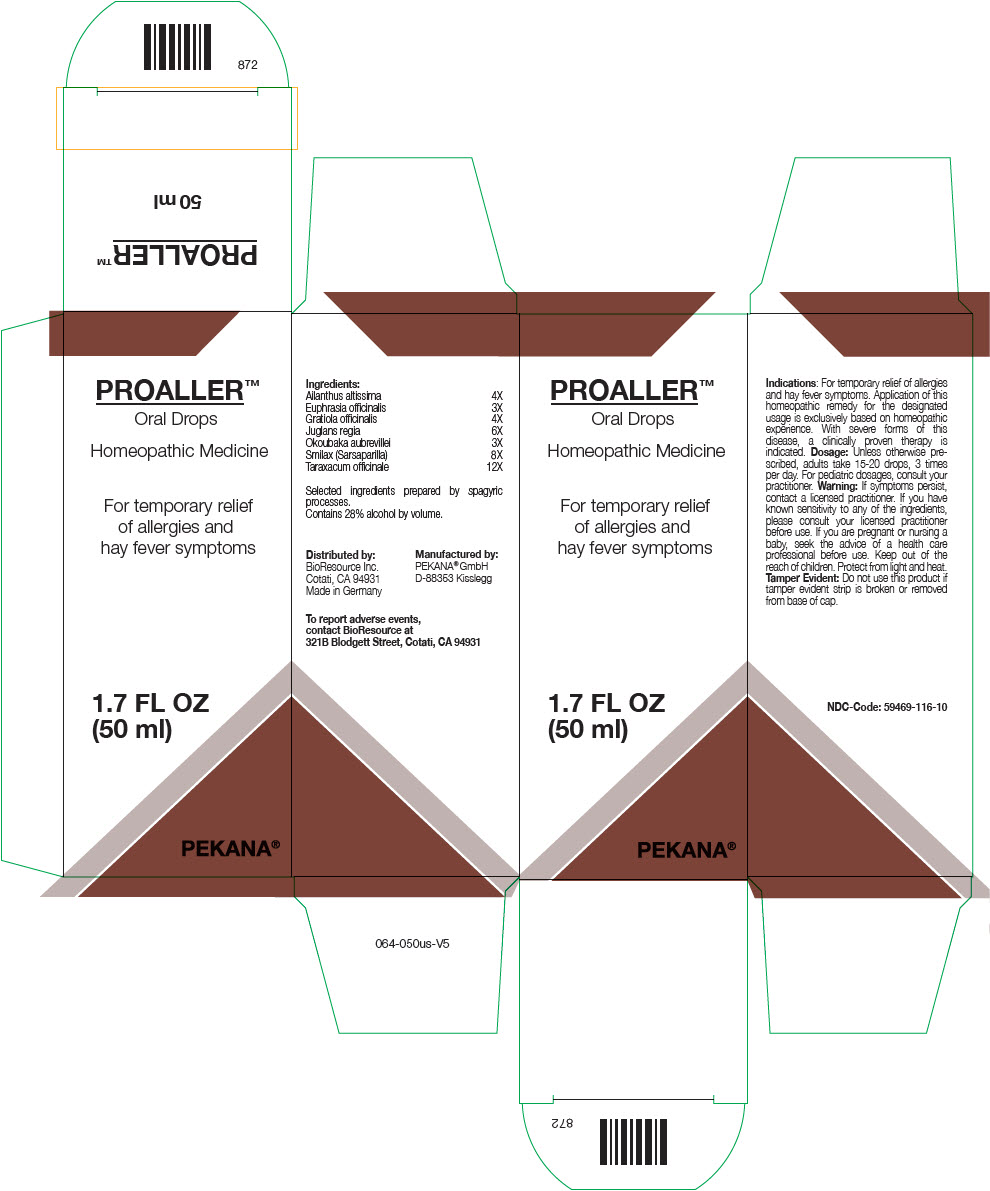 DRUG LABEL: PROALLER
NDC: 59469-116 | Form: SOLUTION/ DROPS
Manufacturer: PEKANA Naturheilmittel
Category: homeopathic | Type: HUMAN OTC DRUG LABEL
Date: 20221219

ACTIVE INGREDIENTS: Ailanthus altissima Whole 4 [hp_X]/50 mL; Okoubaka aubrevillei Bark 3 [hp_X]/50 mL; Euphrasia Stricta 3 [hp_X]/50 mL; GRATIOLA OFFICINALIS WHOLE 4 [hp_X]/50 mL; Juglans regia Whole 6 [hp_X]/50 mL; Smilax Ornata Root 8 [hp_X]/50 mL; Taraxacum officinale Whole 12 [hp_X]/50 mL
INACTIVE INGREDIENTS: Water; Alcohol

PROALLER™

ACTIVE INGREDIENT

Ingredients:
Ailanthus altissima | 4X
Euphrasia officinalis | 3X
Gratiola officinalis | 4X
Juglans regia | 6X
Okoubaka aubrevillei | 3X
Smilax (Sarsaparilla) | 8X
Taraxacum officinale | 12X

Selected ingredients prepared by spagyric processes.

INACTIVE INGREDIENT

Contains 28% alcohol by volume.

Indications

PURPOSE

For temporary relief of allergies and hay fever symptoms. Application of this homeopathic remedy for the designated usage is exclusively based on homeopathic experience. With severe forms of this disease, a clinically proven therapy is indicated.

Dosage

Unless otherwise prescribed, adults take 15-20 drops, 3 times per day. For pediatric dosages, consult your practitioner.

Warning

If symptoms persist, contact a licensed practitioner. If you have known sensitivity to any of the ingredients, please consult your licensed practitioner before use. If you are pregnant or nursing a baby, seek the advice of a health care professional before use.

Keep out of the reach of children.

STORAGE AND HANDLING

Protect from light and heat.

Tamper Evident

Do not use this product if tamper evident strip is broken or removed from base of cap.

QUESTIONS

To report adverse events, contact BioResource at 321B Blodgett Street, Cotati, CA 94931

Distributed by:
BioResource Inc.
Cotati, CA 94931

Manufactured by:
PEKANA® GmbH
D-88353 Kisslegg

PRINCIPAL DISPLAY PANEL - 50 ml Bottle Box

PROALLER™
Oral Drops

Homeopathic Medicine

For temporary relief
of allergies and
hay fever symptoms

1.7 FL OZ
(50 ml)

PEKANA®